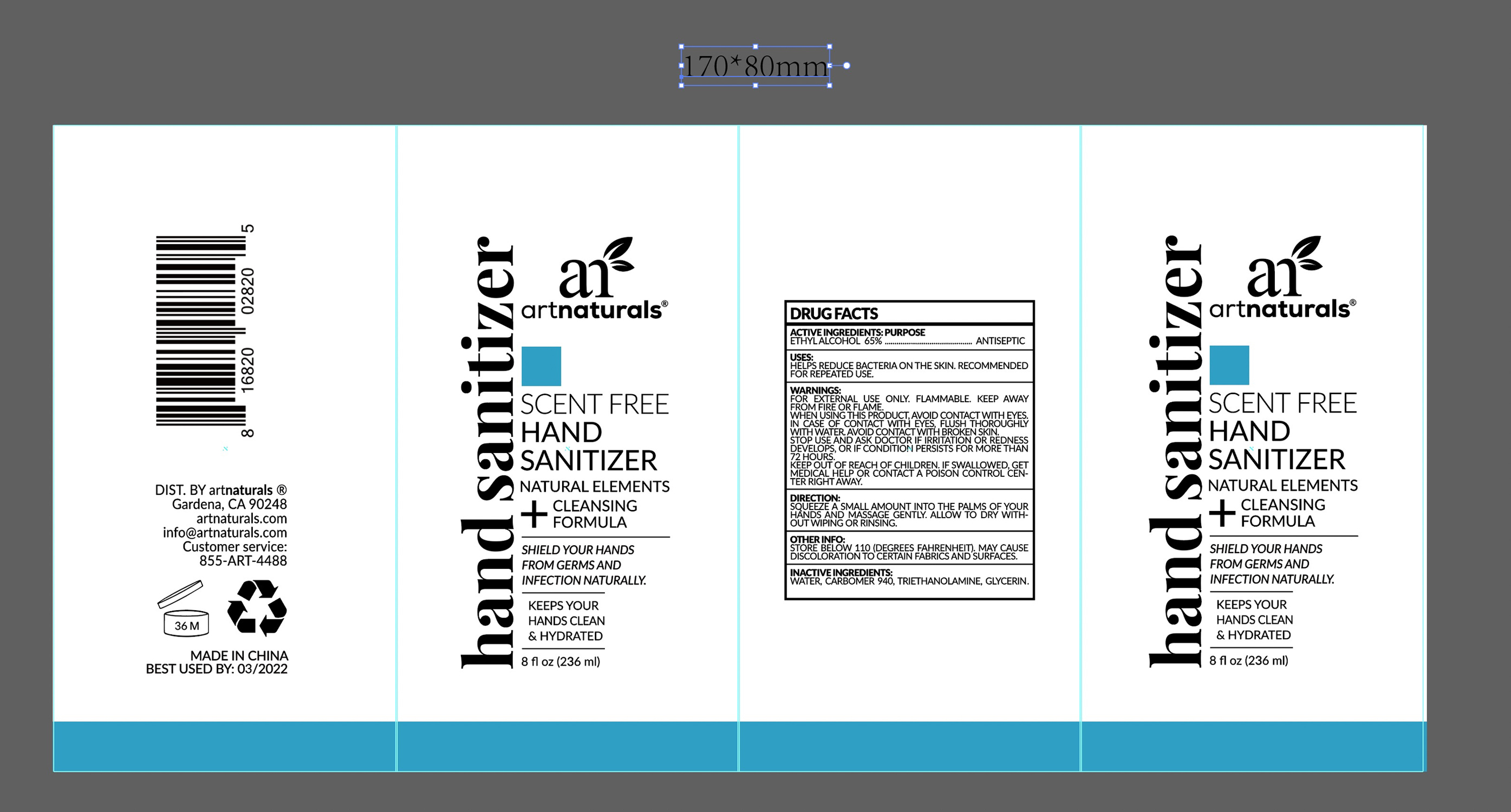 DRUG LABEL: 65% alcohol hand sanitizer (no water)
NDC: 74642-001 | Form: GEL
Manufacturer: Virgin Scent Inc.
Category: otc | Type: HUMAN OTC DRUG LABEL
Date: 20230213

ACTIVE INGREDIENTS: ALCOHOL 65 mL/100 mL
INACTIVE INGREDIENTS: GLYCERIN; ACRYLIC ACID; WATER; TROLAMINE

65% alcohol hand sanitizer (no water)

ACTIVE INGREDIENT

Alcohol 65% v/v. Purpose: Antiseptic

PURPOSE

Antiseptic, Hand Sanitizer

INDICATIONS AND USAGE

HELPS REDUCE BACTERIA ON THE SKIN. RECOMMENDED FOR REPEATED USE.

DOSAGE AND ADMINISTRATION

SQUEEZE A SMALL AMOUNT INTO THE PALMS OF YOUR HANDS AND MASSAGE GENTLY. ALLOW TO DRY WITHOUT WIPING OR RINSING.

WARNINGS

For external use only. Flammable.Keep away from fire or flame.

When using this product, avoid contact with eyes. In case of contact with eyes, flush thoroughly with water. Avoid contact with broken skin.

Stop use and ask doctor if irritation or redness developes. or if condition persists for more than 72 hours

Keep out of reach of children. If swallowed, get medical help or contact a poison control center right away.

INACTIVE INGREDIENT

Water, Carbomer 940, Triethanolamine, Glycerin

OTHER SAFETY INFORMATION

Store below 110 (Degree Fahrenheit). May cause discoloration to certain fabrics and surfaces.

Package Label - Principal Display Panel

236 mL NDC: 74642-001-01